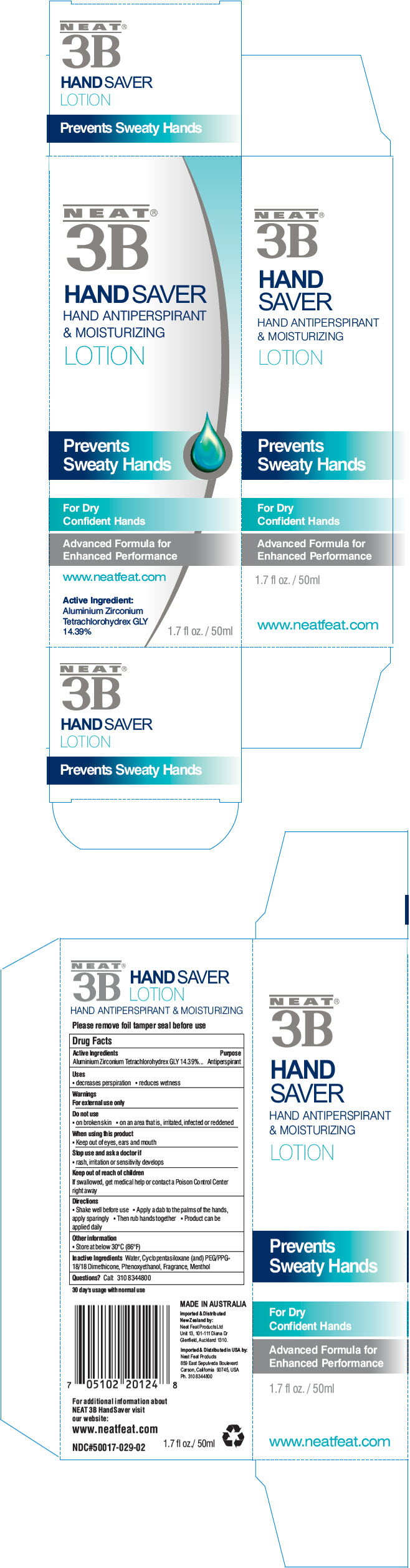 DRUG LABEL: Hand Saver
NDC: 50017-029 | Form: LOTION
Manufacturer: Neat Feat Products Limited
Category: otc | Type: HUMAN OTC DRUG LABEL
Date: 20231101

ACTIVE INGREDIENTS: ALUMINUM ZIRCONIUM TETRACHLOROHYDREX GLY 14.39 g/100 mL
INACTIVE INGREDIENTS: WATER; PEG/PPG-18/18 DIMETHICONE; PHENOXYETHANOL; CYCLOMETHICONE 4; CYCLOMETHICONE 5; MENTHOL, UNSPECIFIED FORM

NEAT® 3B HANDSAVER

Drug Facts

Active Ingredients

Aluminium Zirconium Tetrachlorohydrex GLY 14.39%

Purpose

Antiperspirant

Uses

- decreases perspiration
- reduces wetness

Warnings

For external use only

Do not use

- on broken skin
- on an area that is, irritated, infected or reddened

When using this product

- Keep out of eyes, ears and mouth

Stop use and ask a doctor if

- rash, irritation or sensitivity develops

Keep out of reach of children
If swallowed, get medical help or contact a Poison Control Center right away

Directions

- Shake well before use
- Apply a dab to the palms of the hands, apply sparingly
- Then rub hands together
- Product can be applied daily

Other information

- Store at below 30°C (86°F)

Inactive Ingredients

Water, Cyclotetrasiloxane, Cyclopentasiloxane, PEG/PPG-18/18 Dimethicone, Phenoxyethanol, Fragrance, Menthol

Questions?

Call: 310 8344800

Imported & Distributed
New Zealand by:
Neat Feat Products Ltd
Unit 13, 101-111 Diana Dr
Glenfield, Auckland 1310.

Imported & Distributed in USA by:
Neat Feat Products
859 East Sepulveda Boulevard
Carson, California 90745, USA

PRINCIPAL DISPLAY PANEL - 50 ml Bottle Box

NEAT®
3B

HAND SAVER
HAND ANTIPERSPIRANT
& MOISTURIZING
LOTION

Prevents
Sweaty Hands

For Dry
Confident Hands

Advanced Formula for
Enhanced Performance

www.neatfeat.com

Active Ingredient:
Aluminium Zirconium
Tetrachlorohydrex GLY
14.39%

1.7 fl oz. / 50ml